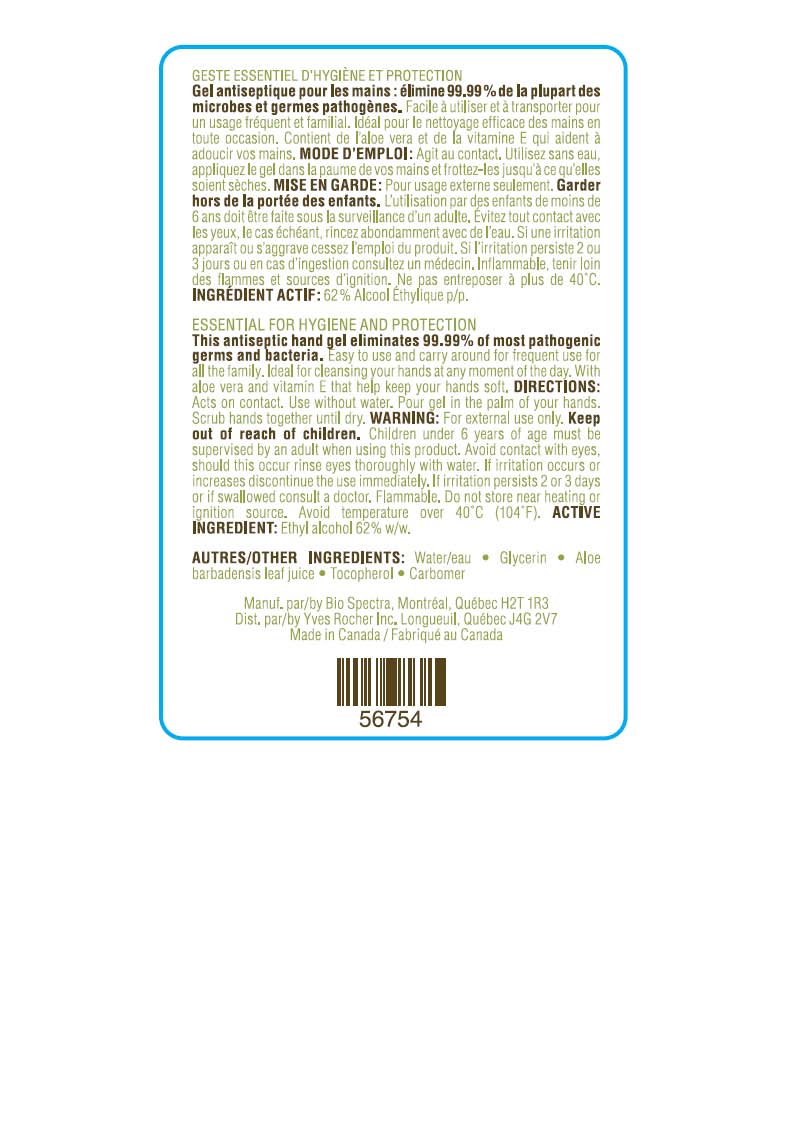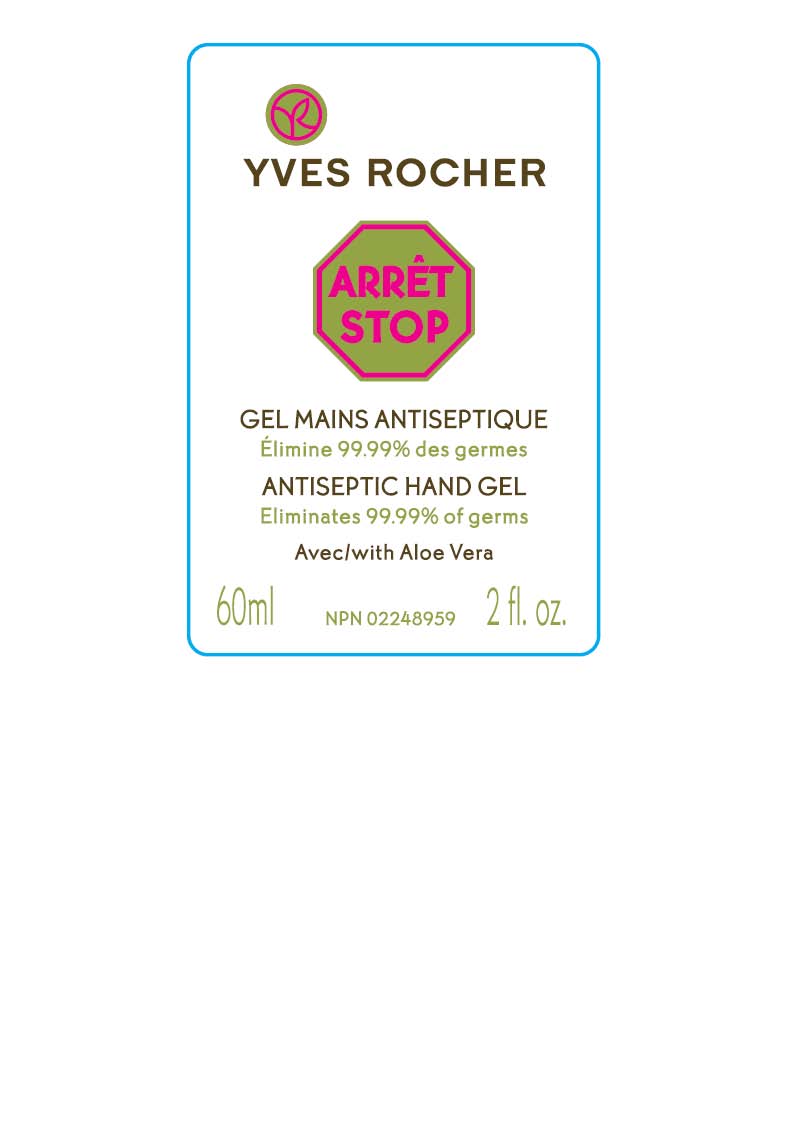 DRUG LABEL: ANTISEPTIC HAND GEL
NDC: 63505-163 | Form: GEL
Manufacturer: YVES ROCHER NORTH AMERICA INC
Category: otc | Type: HUMAN OTC DRUG LABEL
Date: 20091211

ACTIVE INGREDIENTS: ALCOHOL 62 mL/100 mL
INACTIVE INGREDIENTS: WATER 35.23 mL/100 mL; GLYCERIN 2.34 mL/100 mL; ALOE VERA LEAF 0.013 mL/100 mL; ALPHA-TOCOPHEROL 0.007 mL/100 mL; CARBOMER 934 0.410 mL/100 mL

PACKAGE LABEL

ANTISEPTIC HAND GEL

Eliminate 99.99% of germ

With Aloe Vera

60 ml 2 fl. oz.

ACTIVE INGREDIENT:

Ethyl alcohol 62%w/w

Keep out of reach of children. Children under 6 years of age must be supervised by an adult when using this product.

STOP USE

Avoid contact with eyes, should this occur rinse eyes thoroughly with water. If irritation occurs or increases discontinue the use immediately.

ASK DOCTOR

If irritation persists 2 or 3 days or swallowed consult a doctor

PURPOSE

Antiseptic hand gel